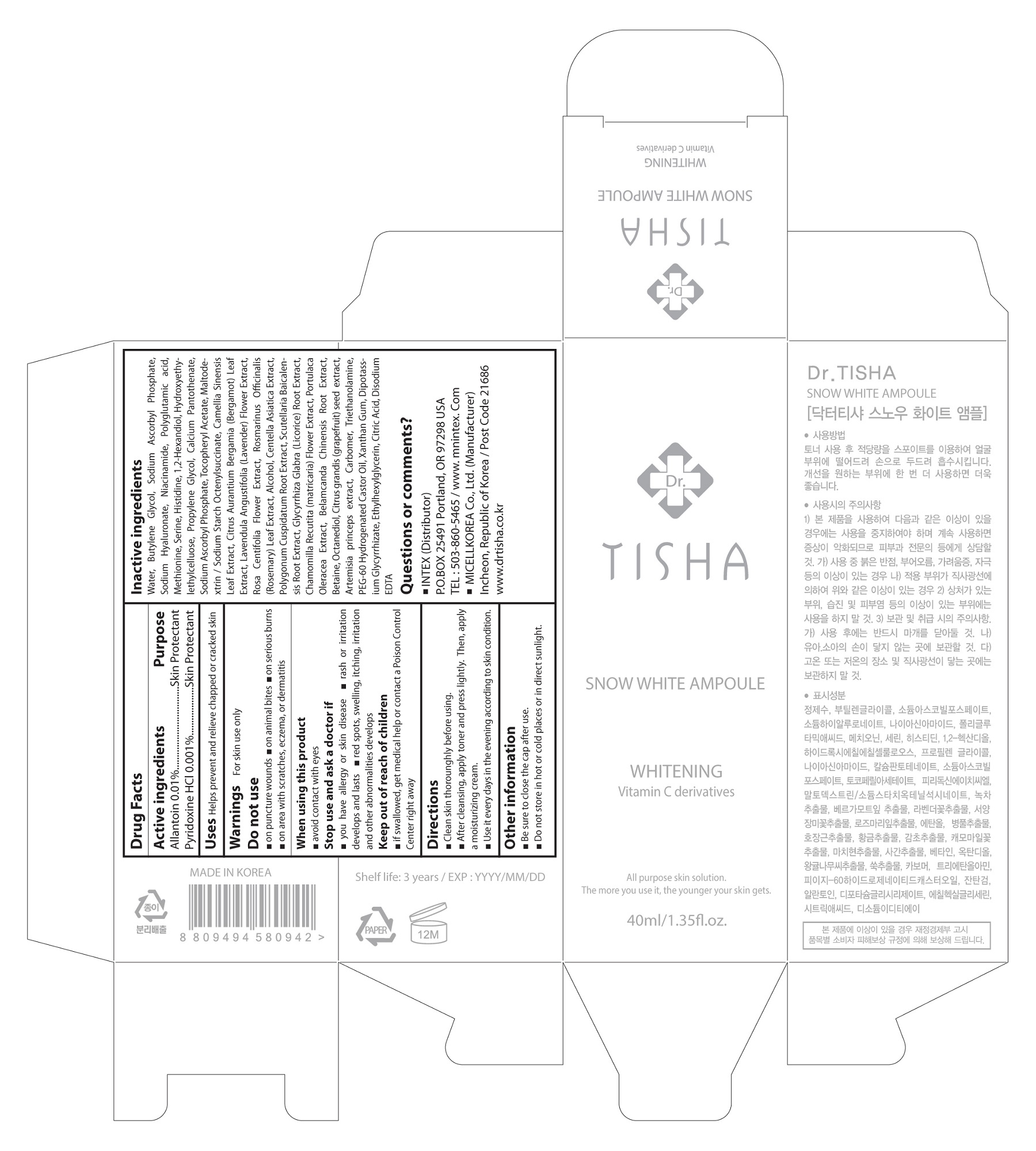 DRUG LABEL: Snow White Ampoule
NDC: 71327-007 | Form: CREAM
Manufacturer: MICELL KOREA CO.,LTD
Category: otc | Type: HUMAN OTC DRUG LABEL
Date: 20170320

ACTIVE INGREDIENTS: Allantoin 0.000004 g/40 mL; PYRIDOXINE HYDROCHLORIDE 0.0000004 g/40 mL
INACTIVE INGREDIENTS: Water; Methionine; Serine; Histidine; Butylene Glycol; Propylene Glycol; Maltodextrin

ACTIVE INGREDIENT

Allantoin (0.01%) - Skin Protectact
Pyridoxine HCl (0.001%) - Skin Protectact

INACTIVE INGREDIENT

Water, Butylene Glycol, Sodium Ascorbyl Phosphate, Sodium Hyaluronate, Niacinamide, Polyglutamic acid, Methionine, Serine, Histidine, 1,2-Hexandiol, Hydroxyethylethylcelluose, Propylene Glycol, Calcium Pantothenate, Sodium Ascorbyl Phosphate, Tocopheryl Acetate, Maltodextrin / Sodium Starch Octenylsuccinate, Camellia Sinensis Leaf Extract, Citrus Aurantium Bergamia (Bergamot) Leaf Extract, Lavendula Angustifolia (Lavender) Flower Extract, Rosa Centifolia Flower Extract, Rosmarinus Officinalis (Rosemary) Leaf Extract, Alcohol, Centella Asiatica Extract, Polygonum Cuspidatum Root Extract, Scutellaria Baicalensis Root Extract, Glycyrrhiza Glabra (Licorice) Root Extract, Chamomilla Recutita (matricaria) Flower Extract, Portulaca Oleracea Extract, Belamcanda Chinensis Root Extract, Betaine, Octanediol, Citrus grandis (grapefruit) seed extract, Artemisia princeps extract, Carbomer, Triethanolamine, PEG-60 Hydrogenated Castor Oil, Xanthan Gum, Dipotassium Glycyrrhizate, Ethylhexylglycerin, Citric Acid, Disodium EDTA

PURPOSE

Skin Protectact

WARNINGS

For skin use only.
Do not use
 on puncture wounds  on animal bites  on serious burns  on area with scratches, eczema, or dermatitis
When using this product
 avoid contact with eyes
Stop use and ask a doctor if
 you have allergy or skin disease
 rash or irritation develops and lasts
 red spots, swelling, itching, irritation and other abnormalities develops

KEEP OUT OF REACH OF CHILDREN SECTION

 if swallowed, get medical help or contact a Poison Control Center right away

INDICATIONS & USAGE SECTION

 Clean skin thorounghly before using
 After cleansing, apply toner and press lightly. Then, apply a moisturizing cream
 Use it every days in the evening according to skin condition

DOSAGE & ADMINISTRATION SECTION

 Clean skin thorounghly before using
 After cleansing, apply toner and press lightly. Then, apply a moisturizing cream
 Use it every days in the evening according to skin condition